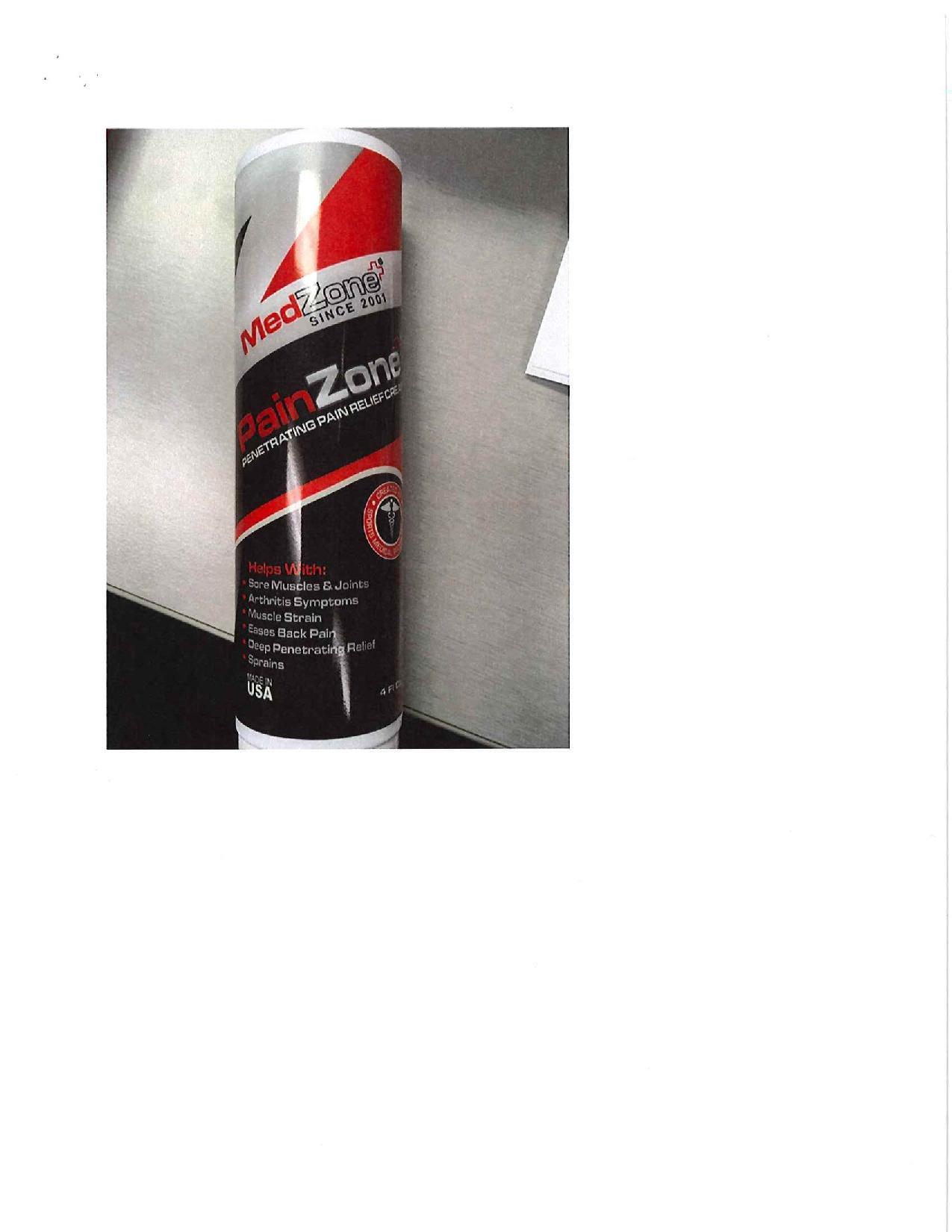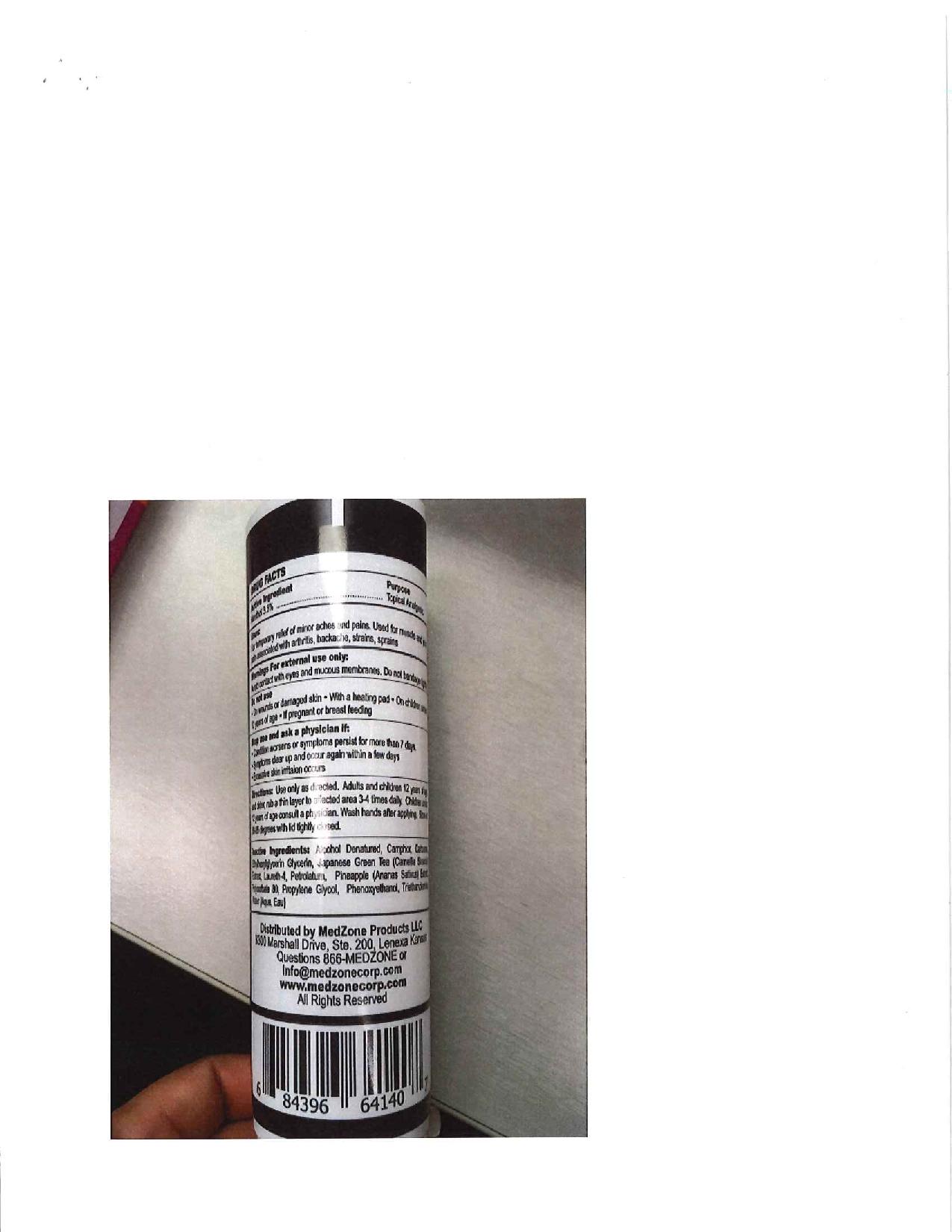 DRUG LABEL: PainZone Light
NDC: 70338-651 | Form: CREAM
Manufacturer: MEDZONE PRODUCTS LLC
Category: otc | Type: HUMAN OTC DRUG LABEL
Date: 20201226

ACTIVE INGREDIENTS: MENTHOL 35 mg/1 g
INACTIVE INGREDIENTS: CAMPHOR (NATURAL); GREEN TEA LEAF; CARBOMER 940; GLYCERIN; PETROLATUM; LAURETH-4; PHENOXYETHANOL; ETHYLHEXYLGLYCERIN; TRIETHANOLAMINE DODECYLBENZENESULFONATE; PROPYLENE GLYCOL 1-(2-METHYLBUTYRATE); ALCOHOL; PINEAPPLE; WATER; POLYSORBATE 80

PainZone Light Cream

Active Ingredient

Active Ingredient | Use
Menthol 3.5% | Topical Analgesic

Uses

- For temporary relief of minor aches and pains. Used for muscle and joint pain associated with arthritis, backache, strains, sprains

Do Not Use

- On wounds or damaged skin
- With a heating pad
- On children under 12 years of age
- If pregnant or breast feeding

Stop use and ask a physicinan if:

Stop use and ask a physician if:

- Conditiion worsens or symtops persist for more than 7 days
- Symptoms clear up and occur again within a few days
- Excessive skin irritation occurs

Directions

Use only as directed
Adults and children 12 years of age and older, rub a thin layer to affected area 3-4 times daily
Children under 12 years of age consult a physician
Wash hands after applying

Storage

Store at 68-86 degrees with lid tightly closed

Inactive Ingredient

Alcohol Denaturated, Camphor, Carbomer, Ethylhexylglycerin, Glycerin, Jaanese Green tea (Camellia Sinesis) Extract, Laureth-4, Petrolatum, Pineapple (Ananas Sativus) Extract, Polysorbate 80, Propylene Glycol, Phenoxyethanol, Triethanolamine, Water

Warnings For External Use Only:

- Avoid contact with eyes and mucous membranes. Do not bandage tightly

Distributed By

Distributed by: MedZone

Lenexa, Kansas

Ph 913-948-9663

www.medzonecorp.com